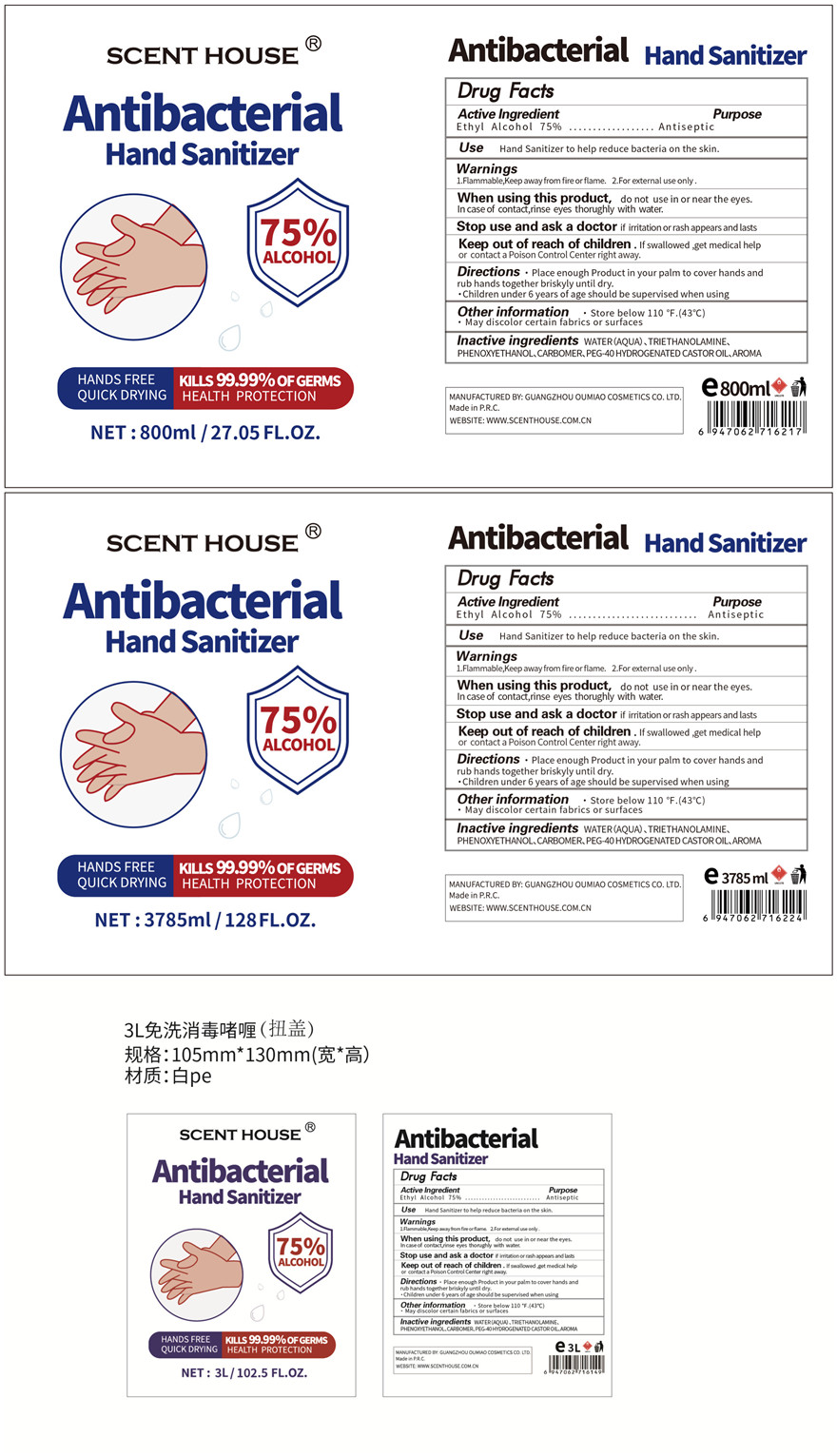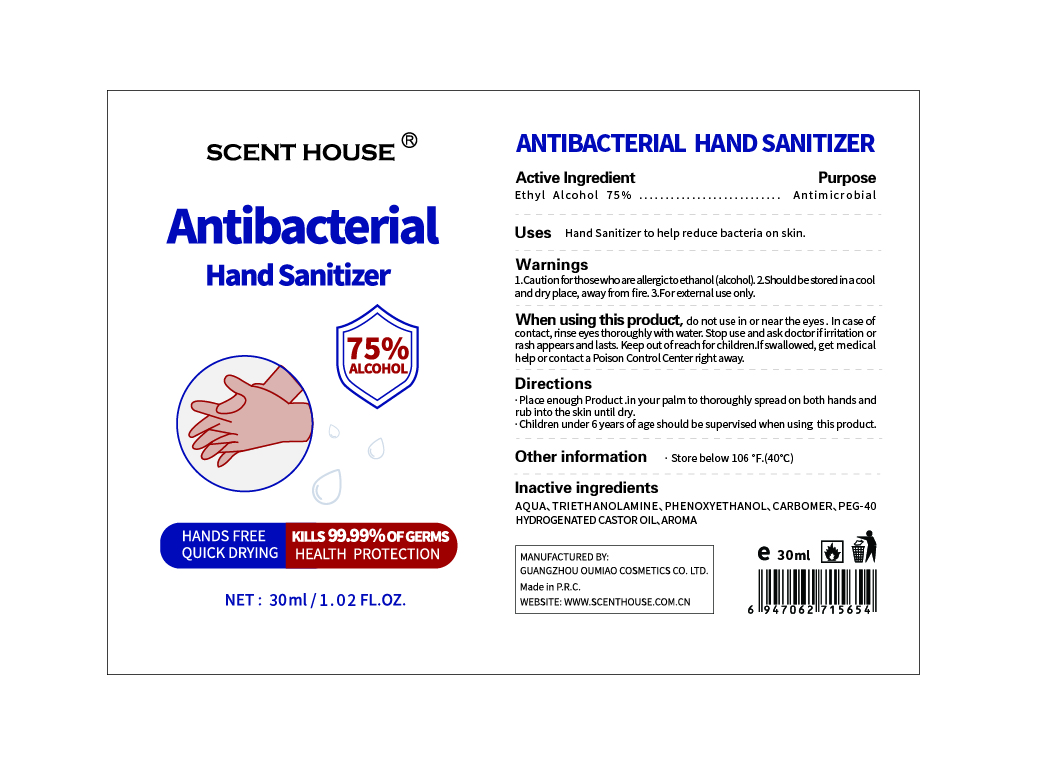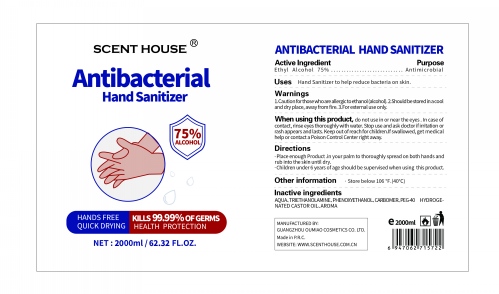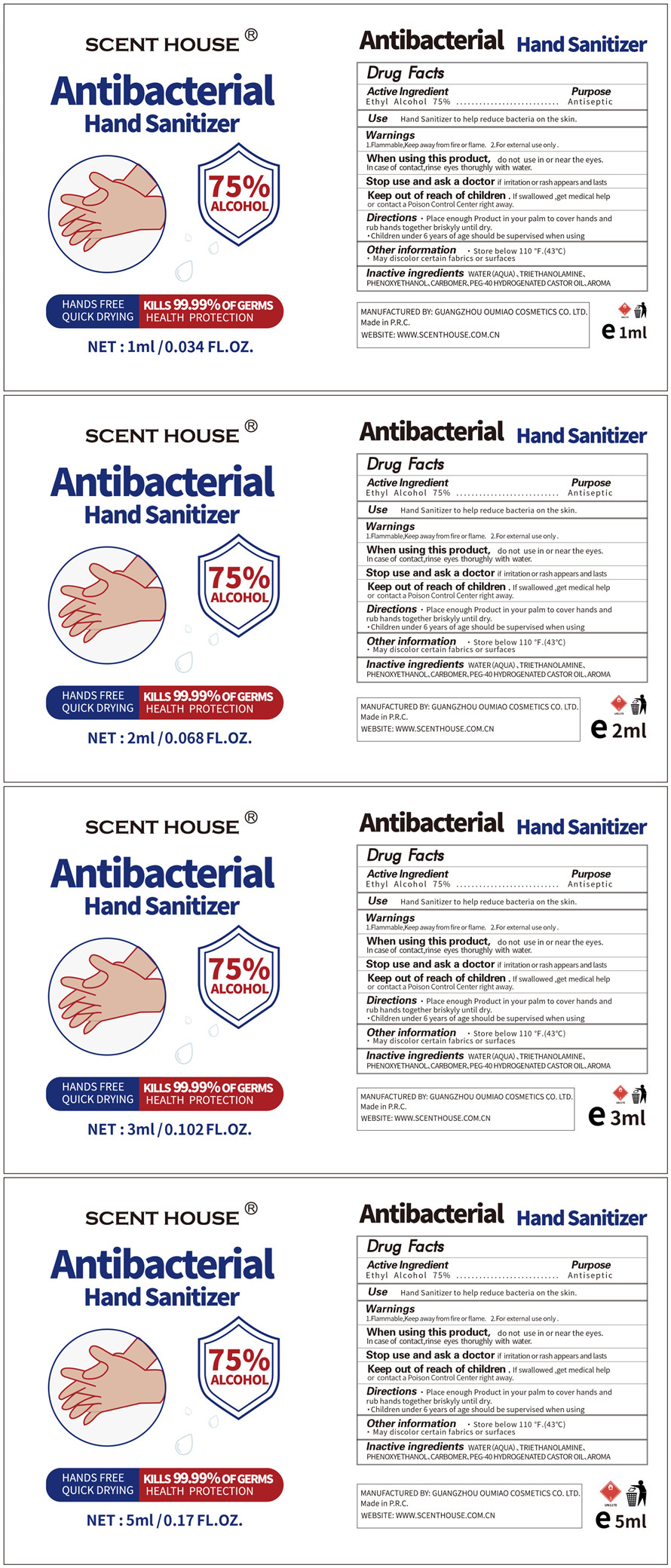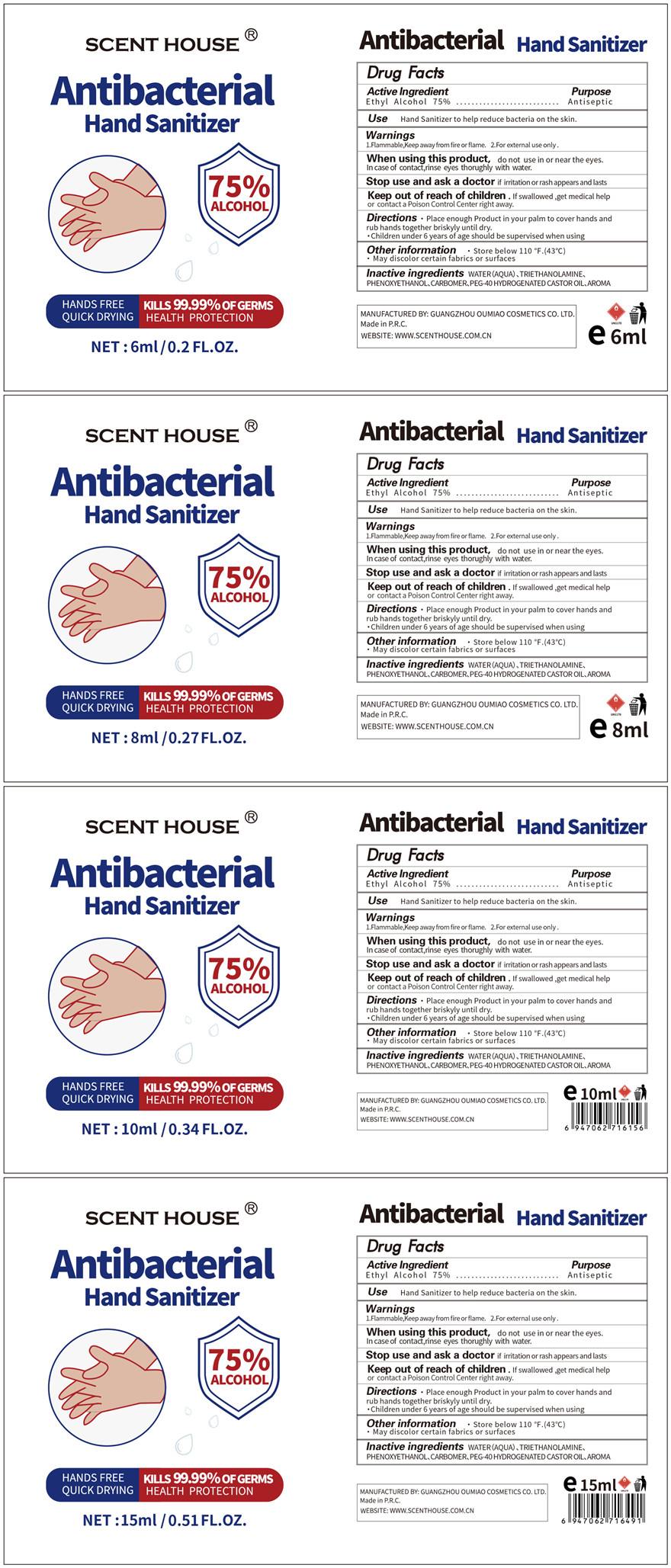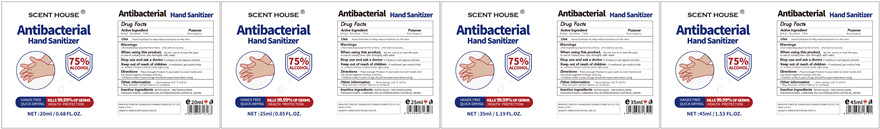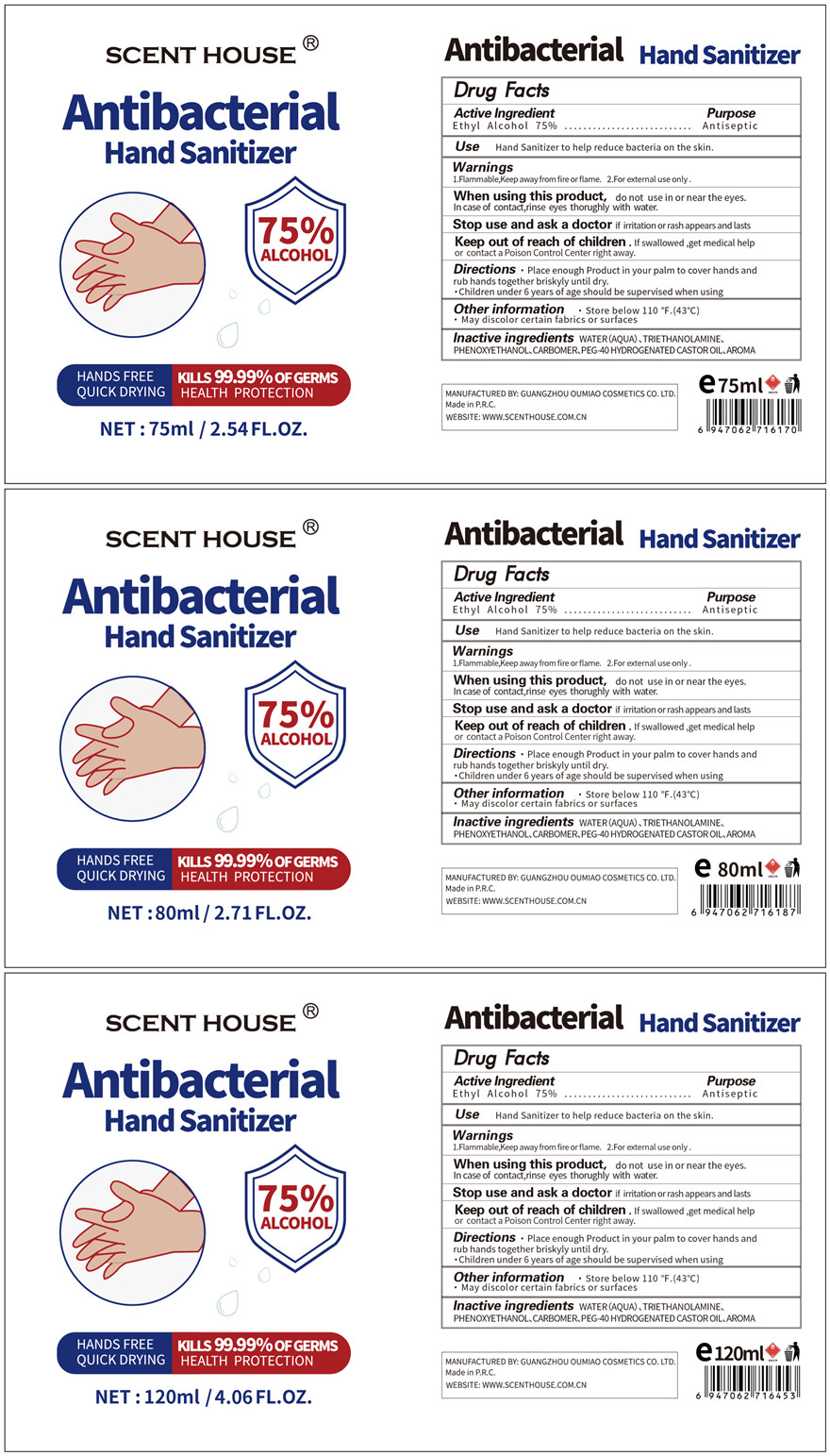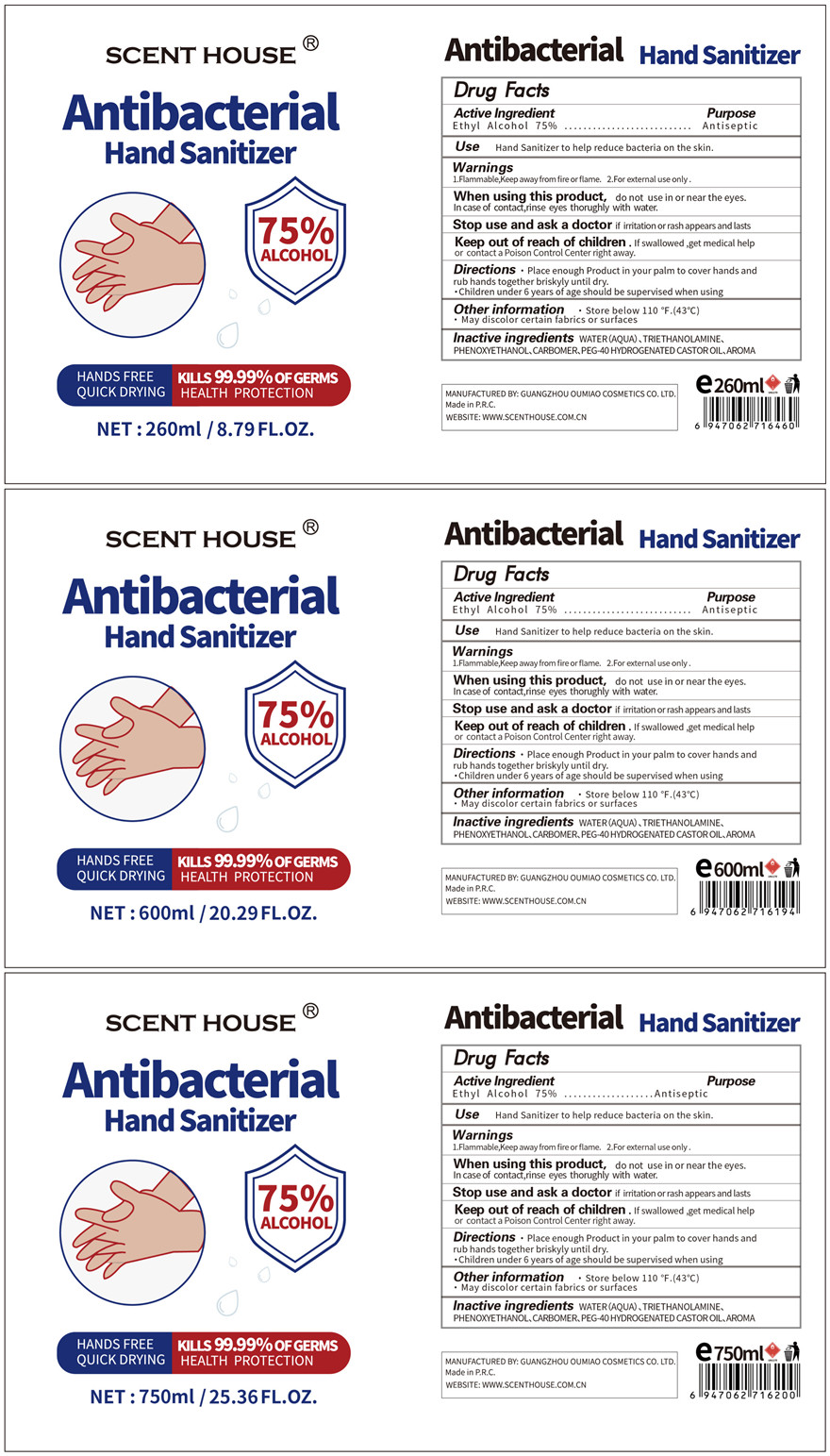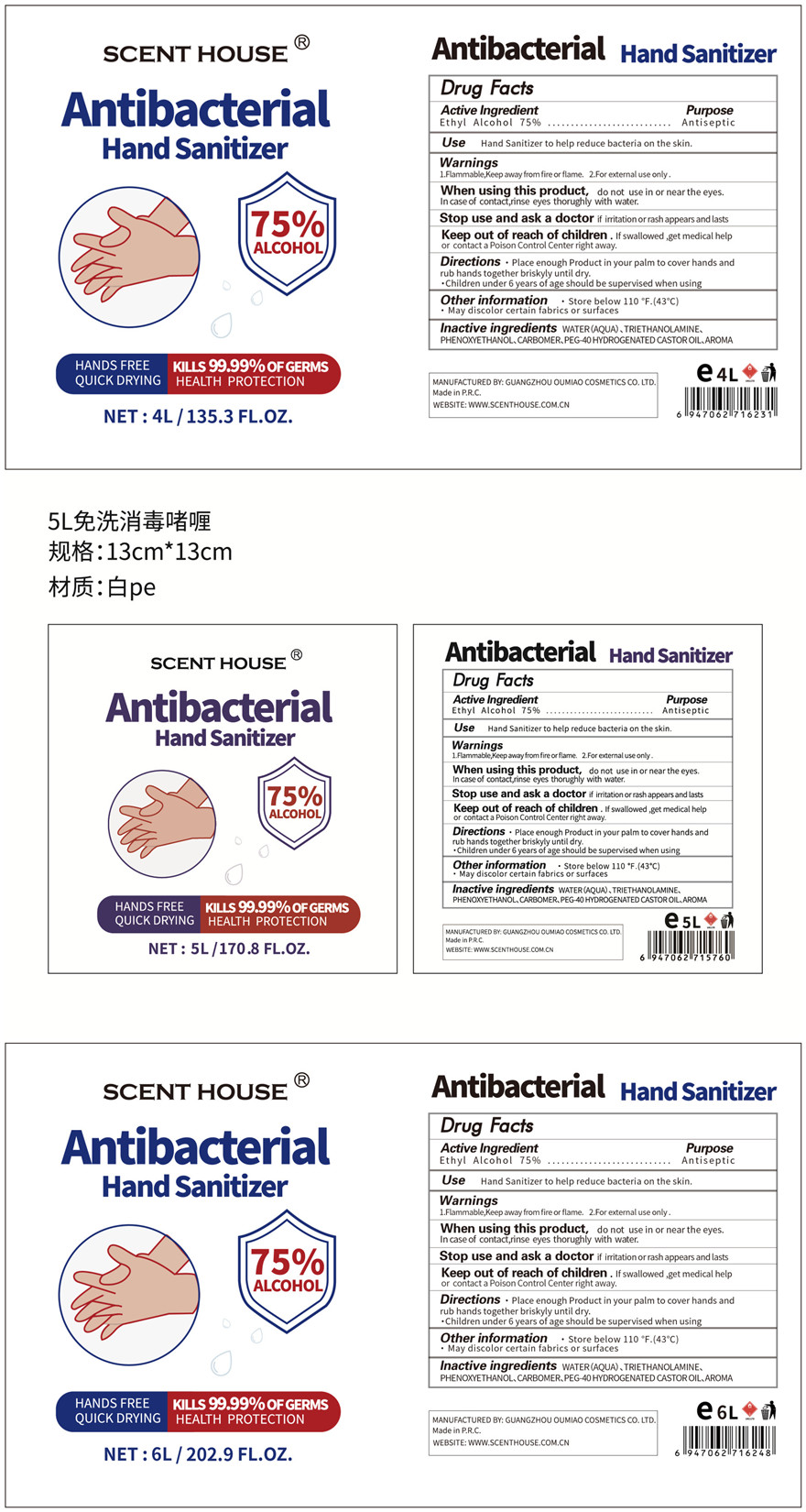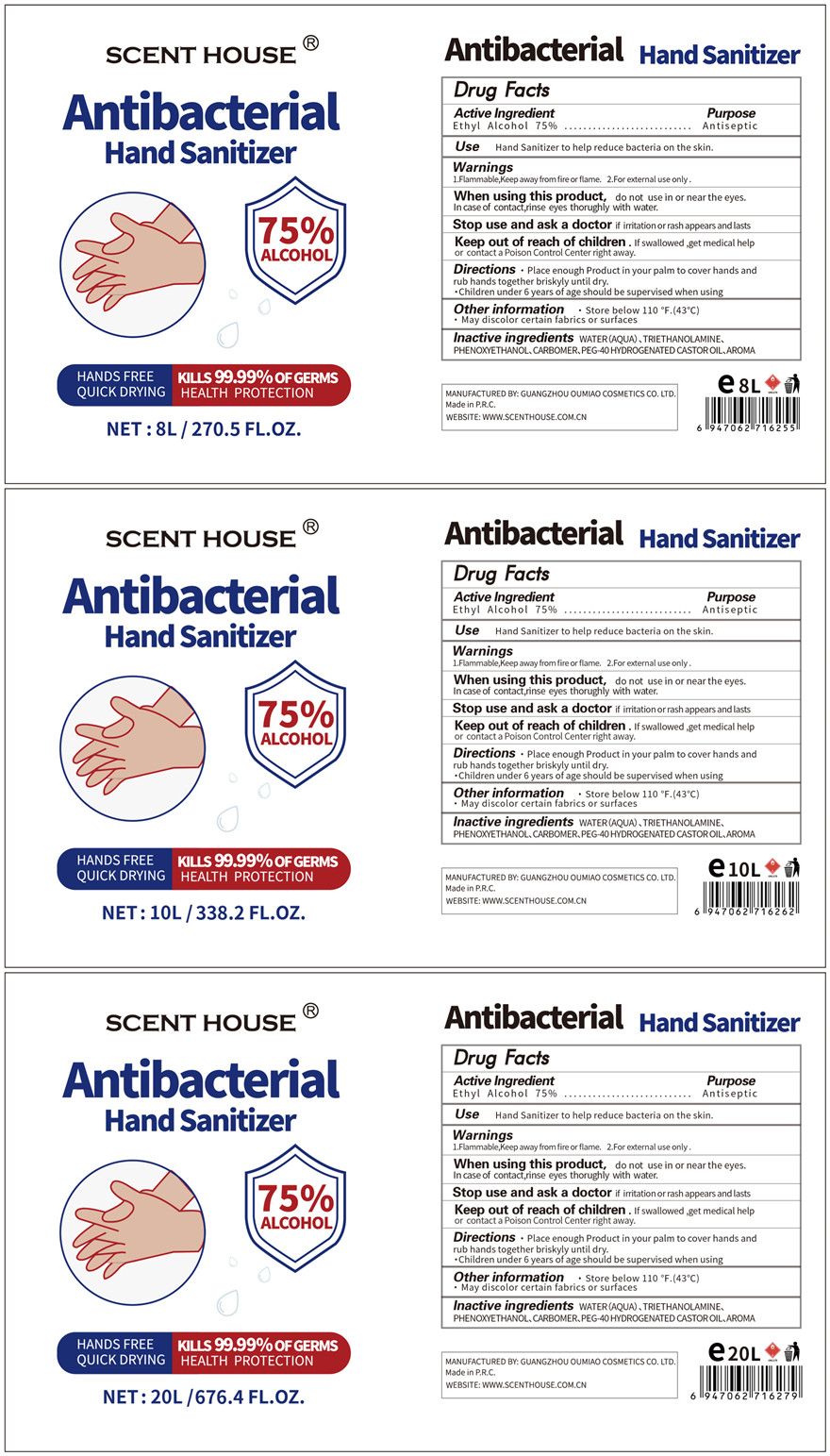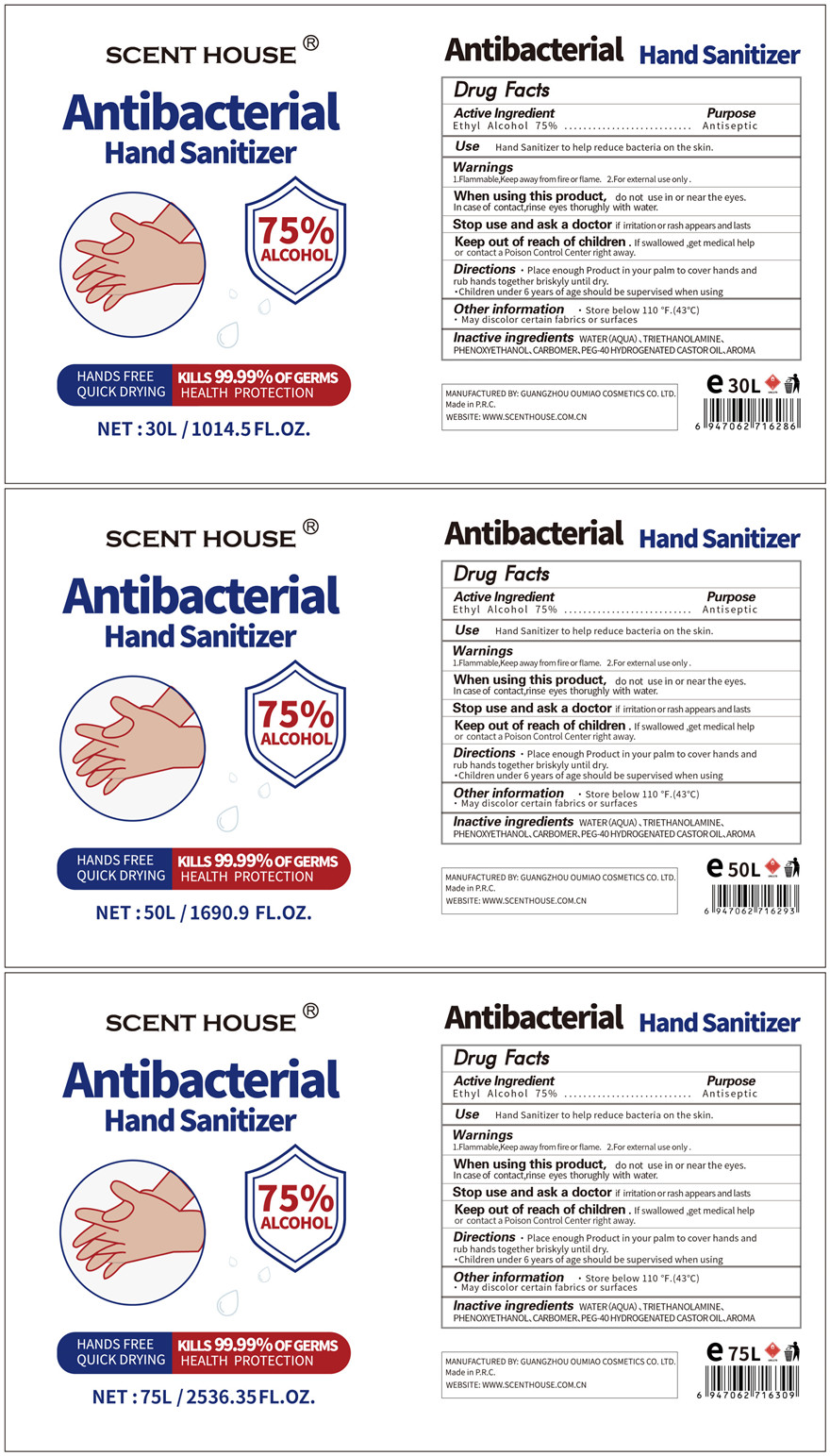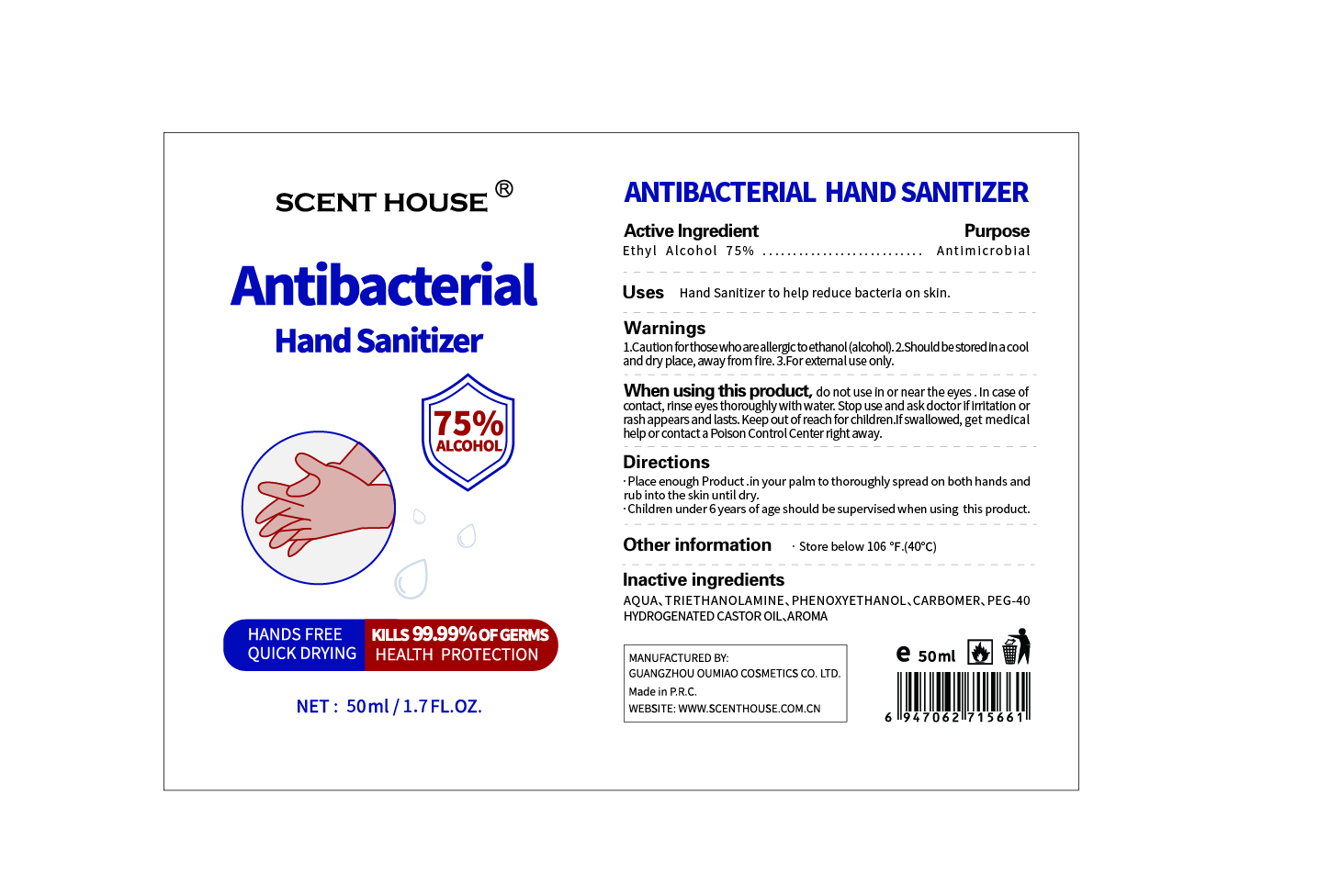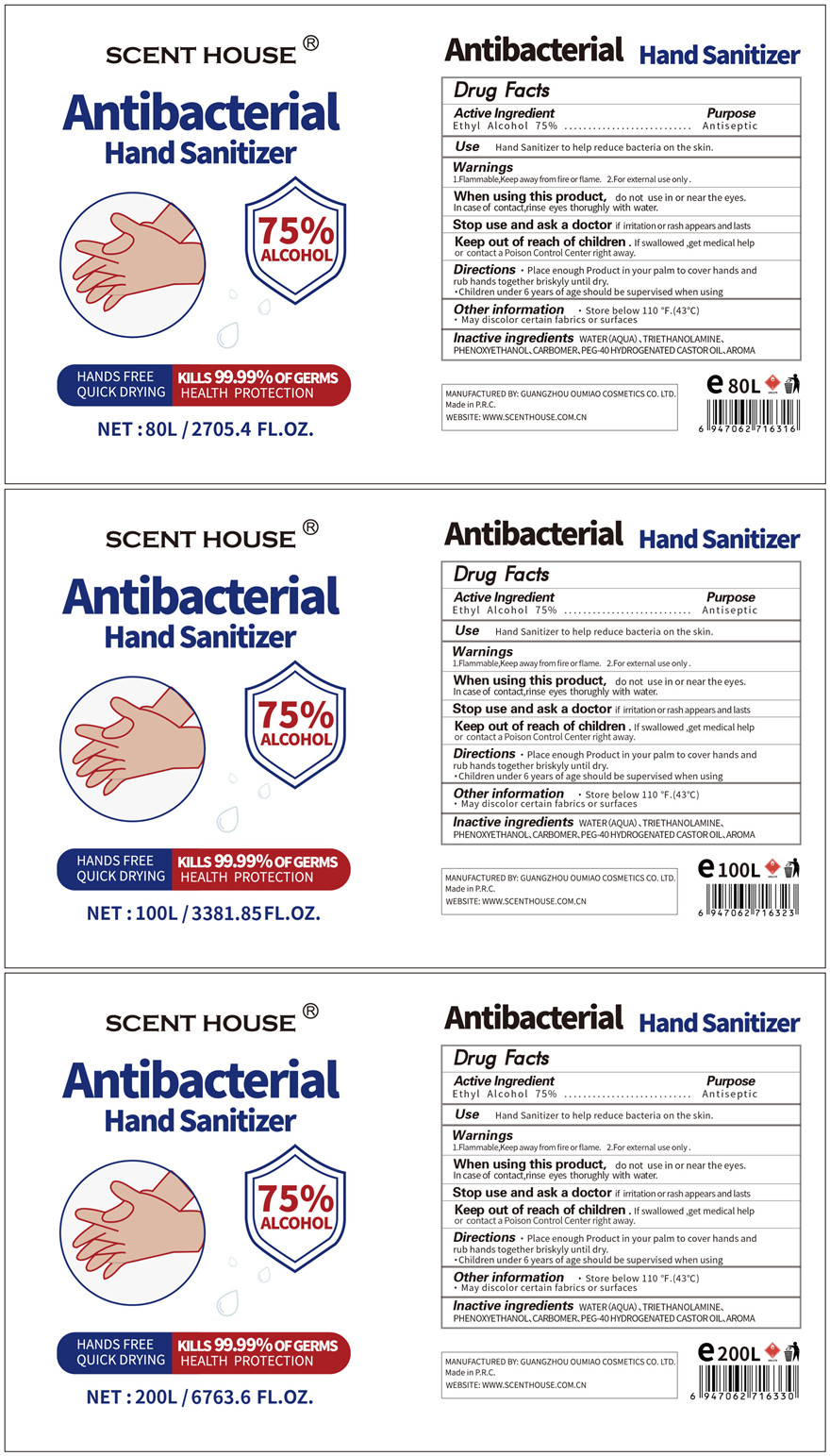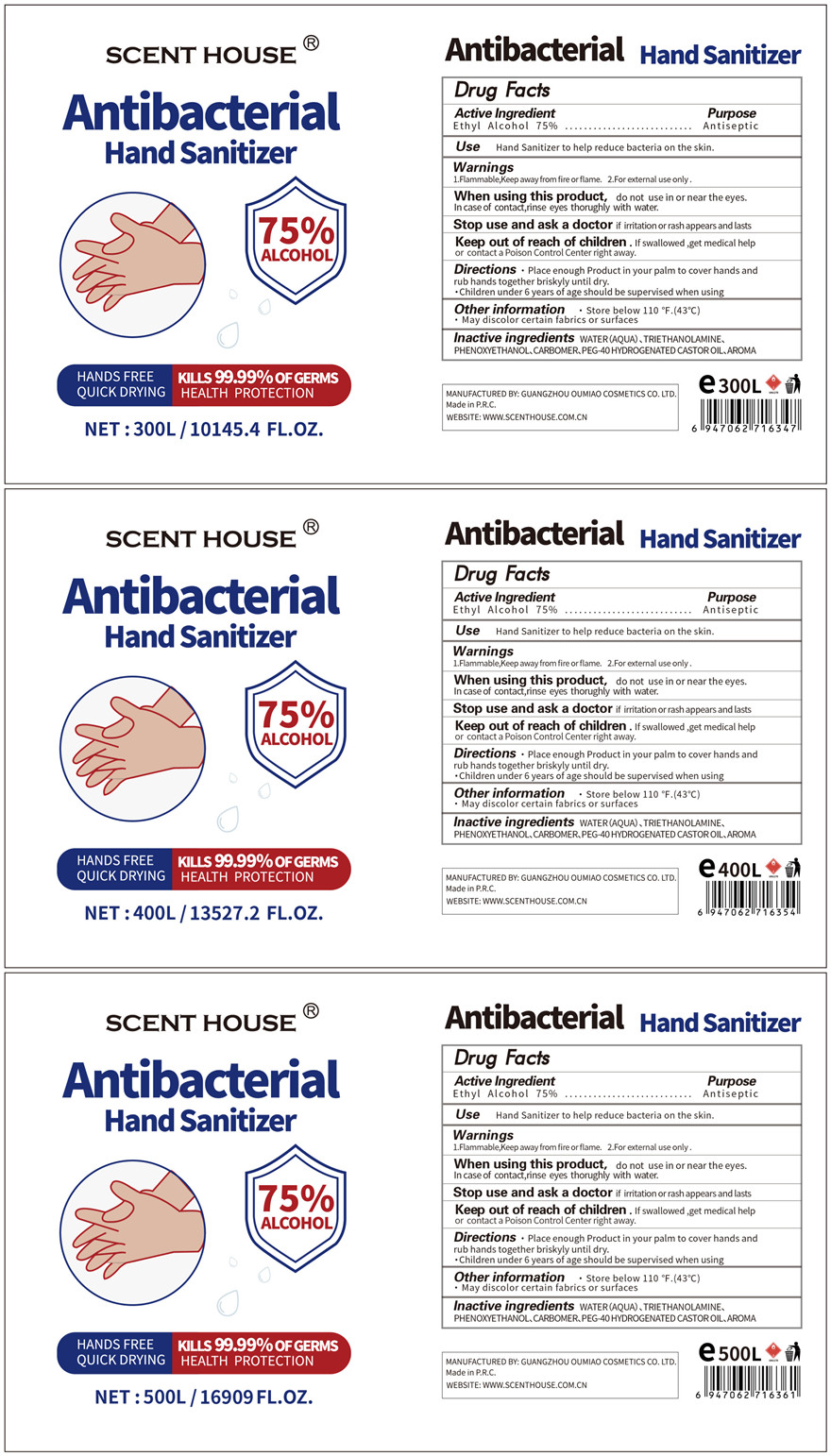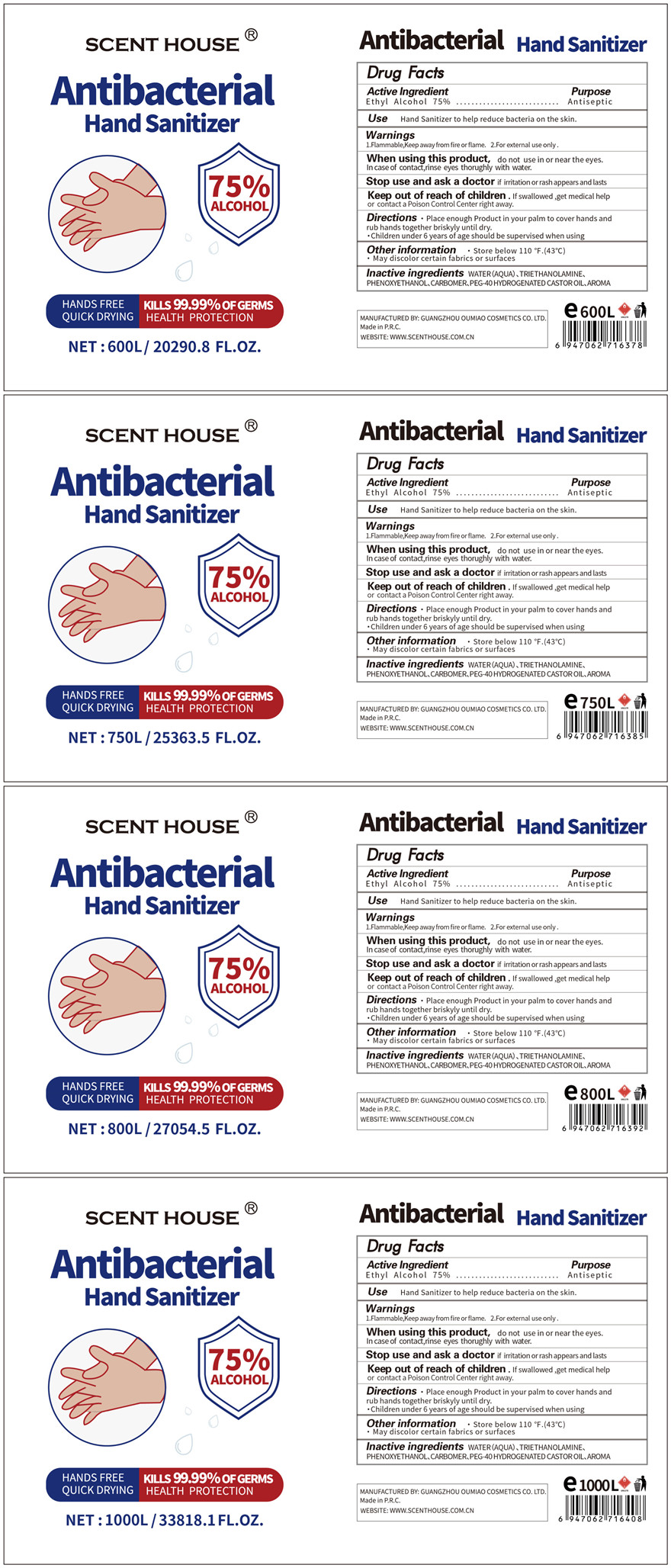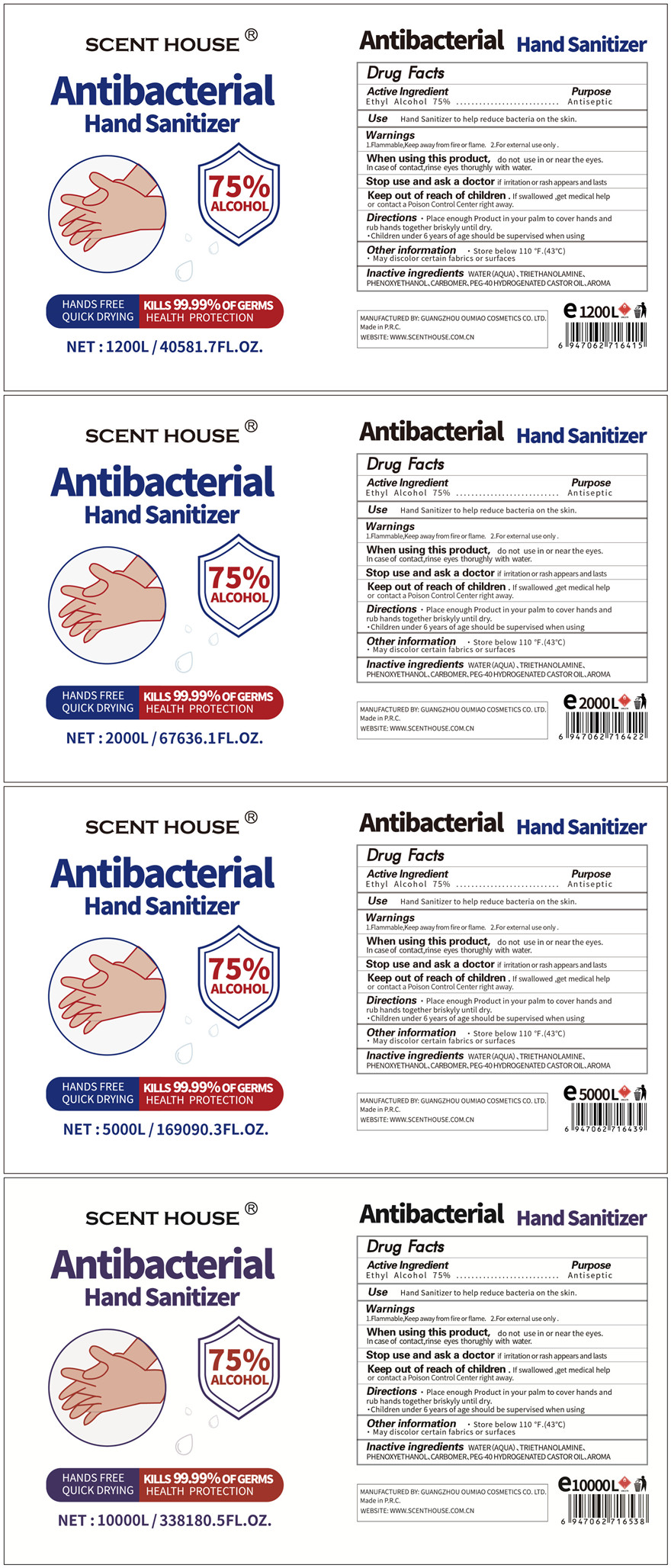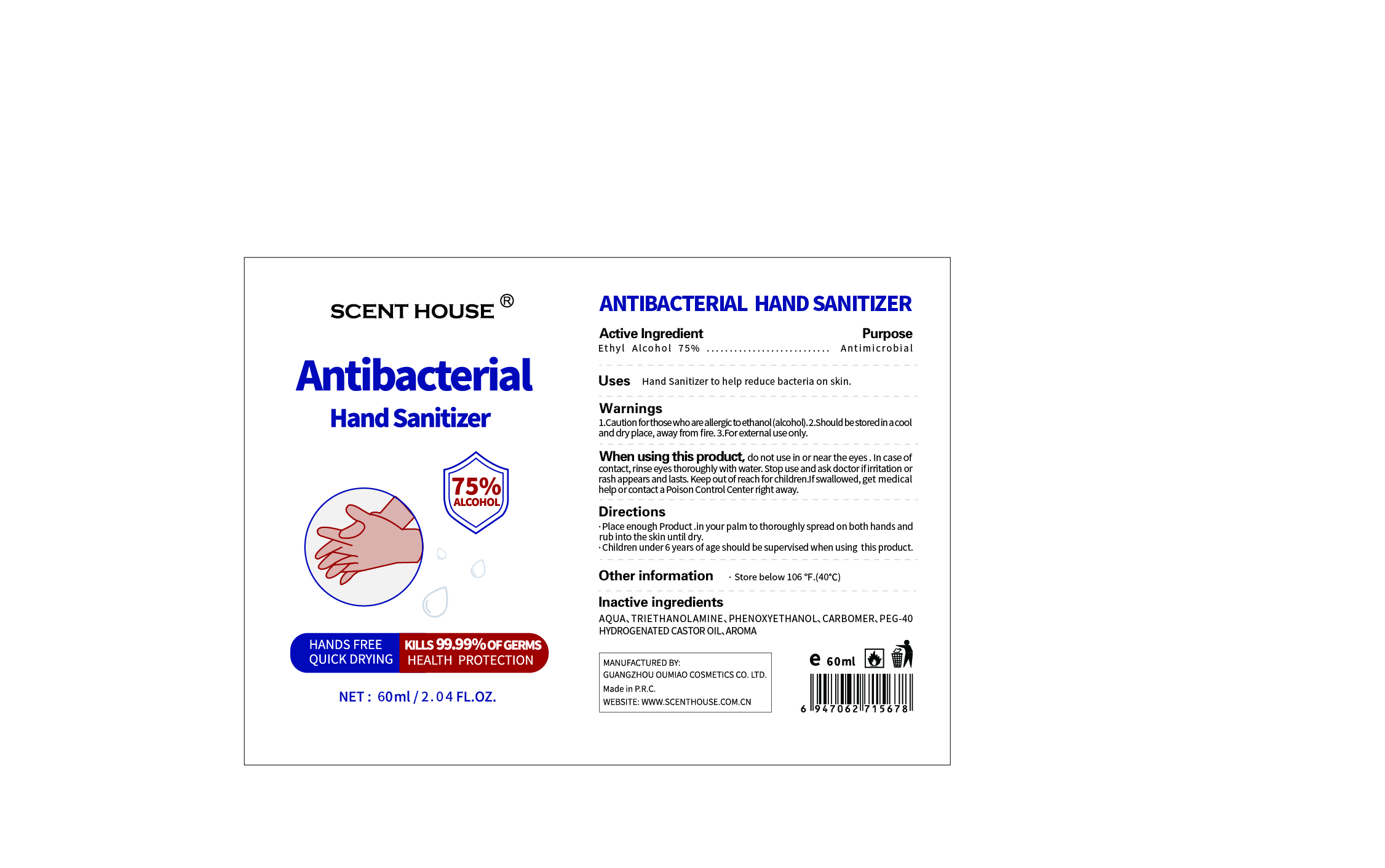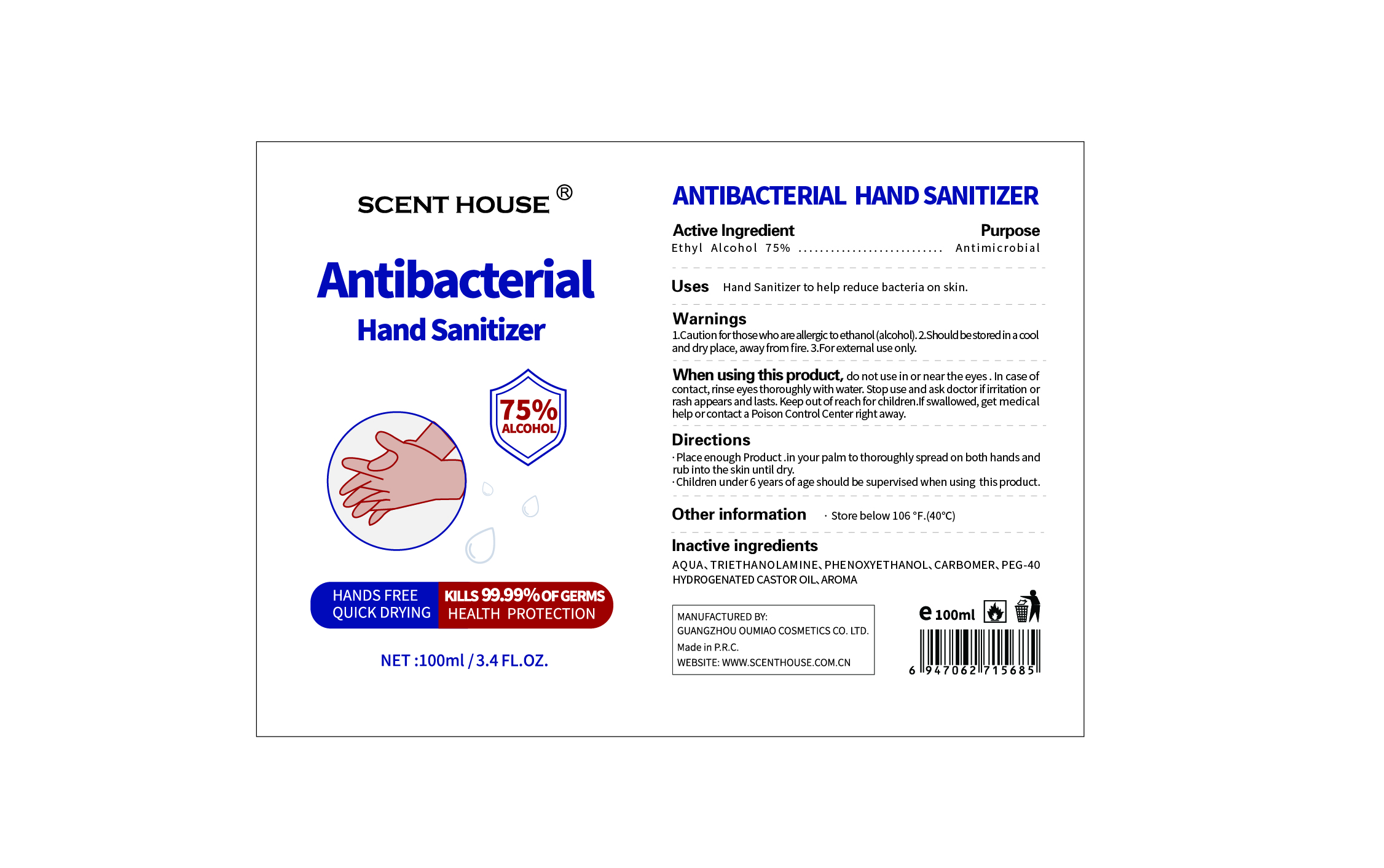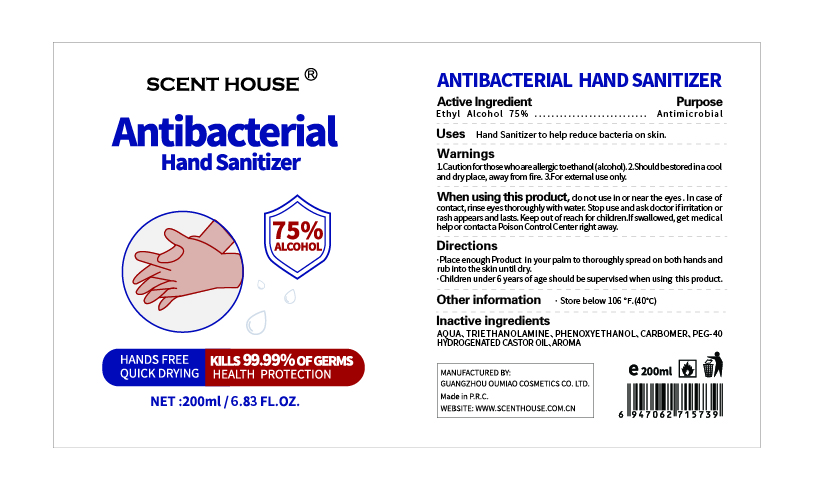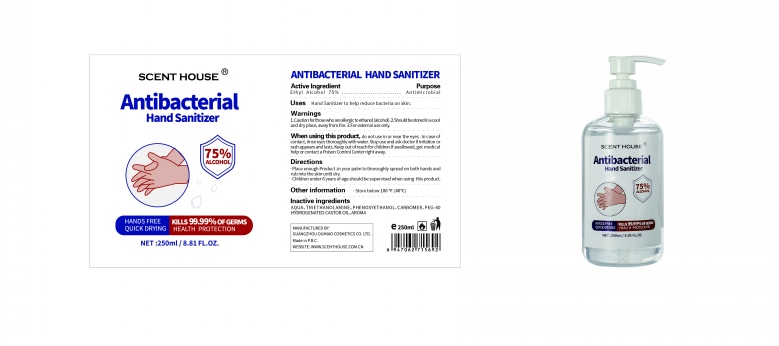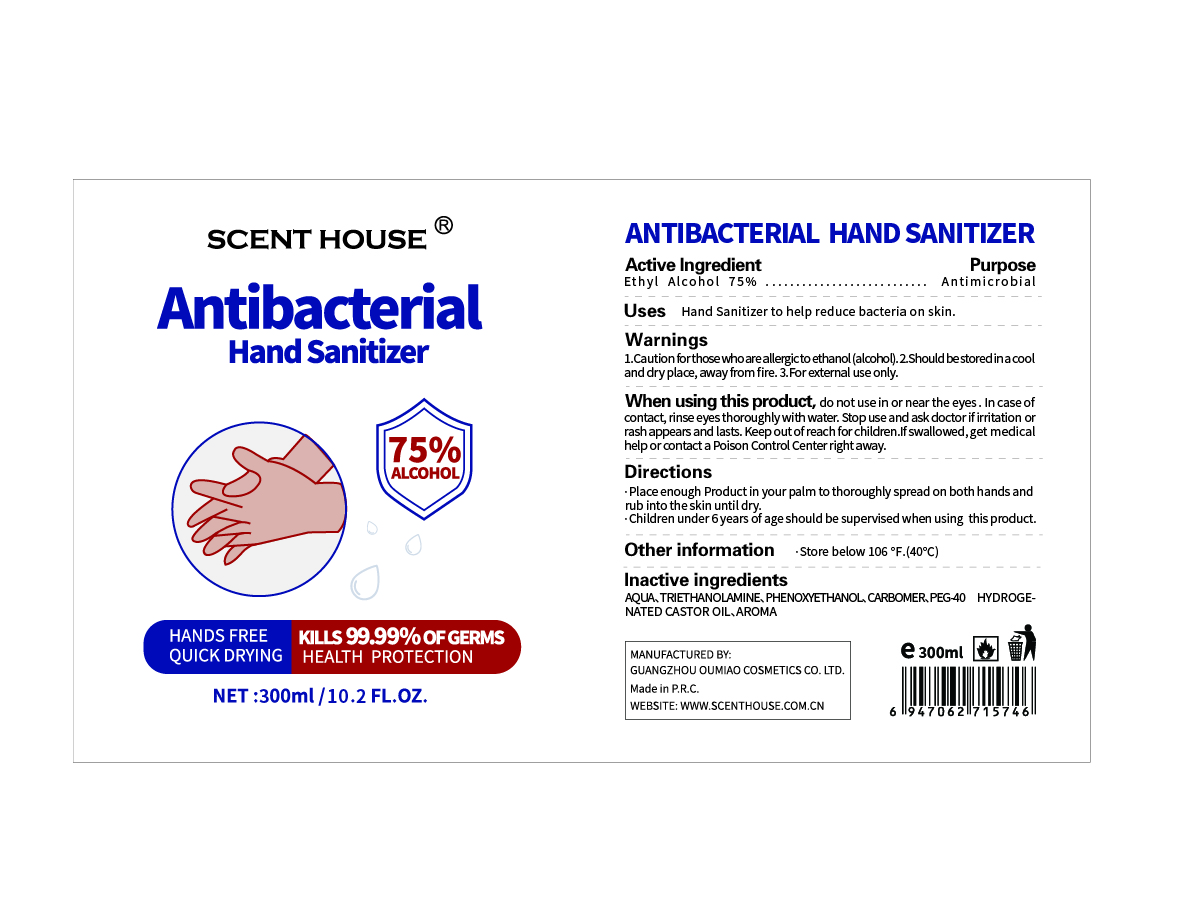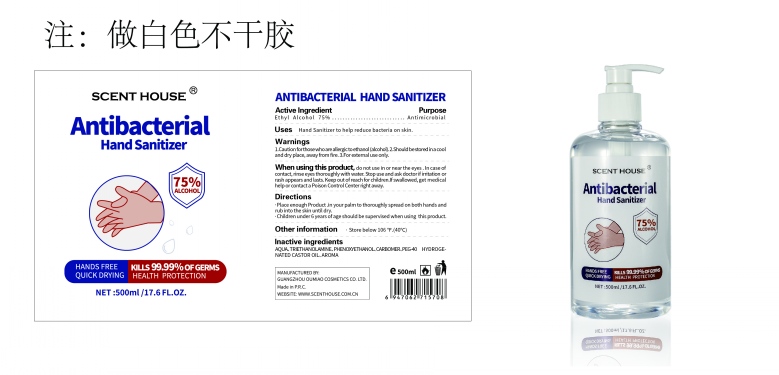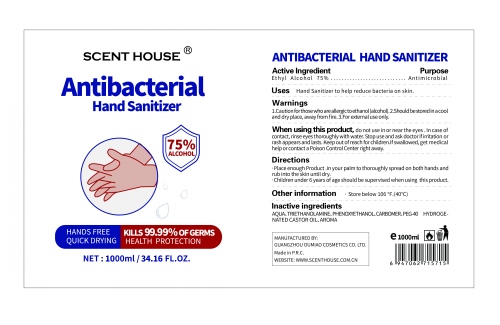 DRUG LABEL: Antibacterial Hand Sanitizer
NDC: 74761-011 | Form: GEL
Manufacturer: Guangzhou Oumiao Cosmetics Co. Ltd. 
Category: otc | Type: HUMAN OTC DRUG LABEL
Date: 20200523

ACTIVE INGREDIENTS: ALCOHOL 75 mL/100 mL
INACTIVE INGREDIENTS: WATER; POLYOXYL 40 HYDROGENATED CASTOR OIL; TROLAMINE; PHENOXYETHANOL; CARBOMER HOMOPOLYMER, UNSPECIFIED TYPE

Antibacterial Hand Sanitizer

Active Ingredient

Ethyl Alcohol 75%.

Purpose

Antimicrobial

Uses

Hand Sanitizer to help reduce bacteria on skin.

Warnings

1.Caution for thosewho are allergic to ethanol(alcohol).

2.Should be stored in a cool and dry place, away from fire.

3.For external use only.

When using this product

do not use in or near the eyes.In case of contact,rinse eyes thoroughly with water.Stop use and ask doctor if irritation or rash appears and lasts.Keep out of reach for children.lf swallowed, get medical help or contact a Poison Control Center right away.

Directions

Place enough Product.in your palm to thoroughly spread on both hands and rub into the skin until dry.

Children under 6 years of age should be supervised when using this product.

Other information

Store below 106°F.(40℃)

Inactive ingredients

AQUA,TRIETHANOLAMINE, PHENOXYETHANOL,CARBOMER,PEG-40 HYDROGENATED CASTOR OIL,AROMA